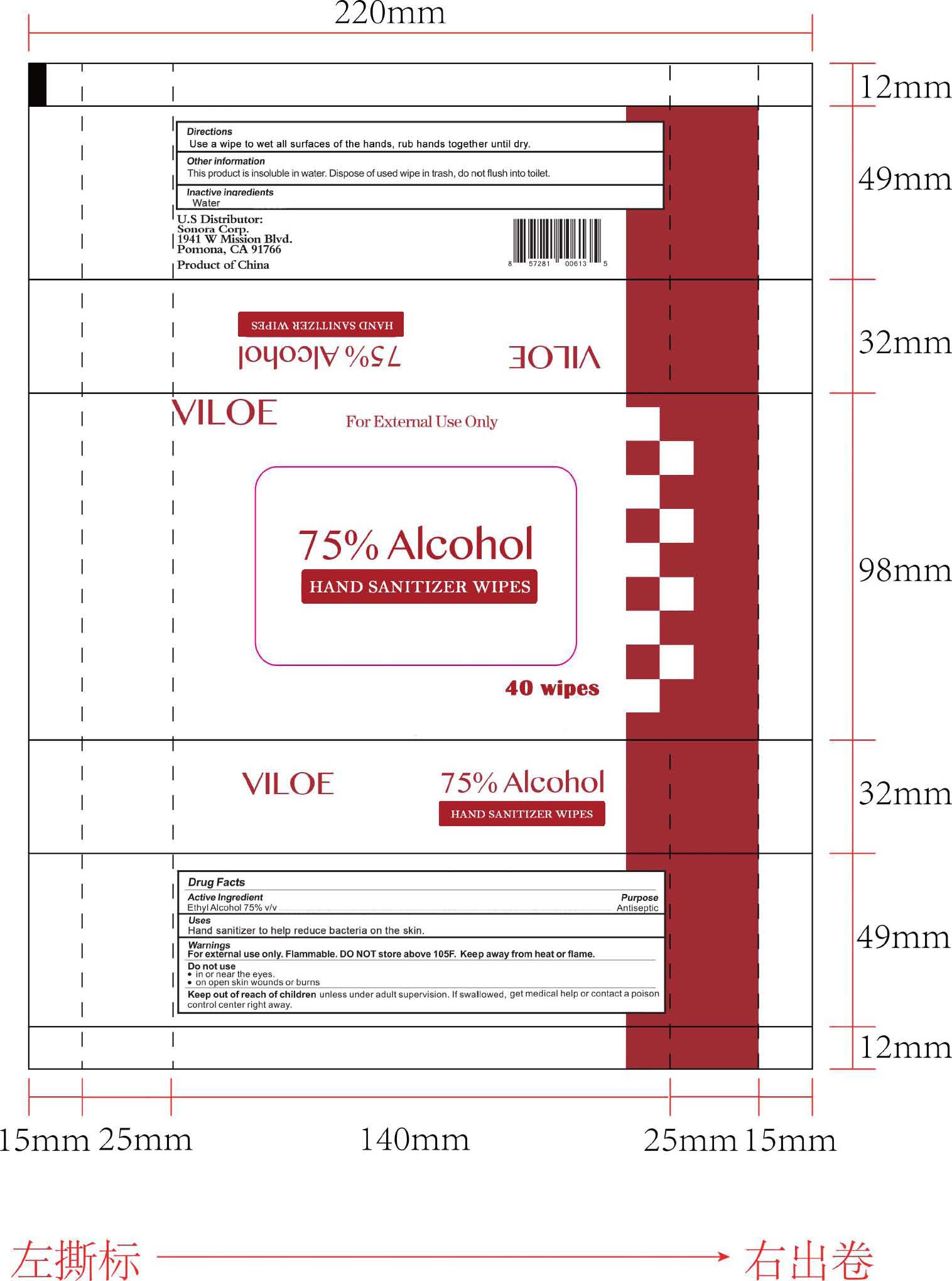 DRUG LABEL: Hand Sanitizer Wipes
NDC: 78410-613 | Form: CLOTH
Manufacturer: Wenzhou Mingwei Paper Co., Ltd.
Category: otc | Type: HUMAN OTC DRUG LABEL
Date: 20200914

ACTIVE INGREDIENTS: ALCOHOL 75 mL/100 1
INACTIVE INGREDIENTS: WATER

Wenzhou Mingwei Paper Co., Ltd.

Active Ingredient

Ethyl Alcohol 75% v/v

Purpose

Ethyl Alcohol - Antiseptic

Uses

Hand Sanitizer to help reduce bacteria on the skin.

Warnings

For external use only. Flammabl. DO NOT store above 105°F. Keep away from heat or flame.

Do not use

- in or near the eyes.
- on open skin wounds or burns.

Keep out of reach of children unless under adult supervision. If swallowed, get medical help or contact a poison control center right away.

Directions

Use a wipe to wet all surfaces of the hands, rub hands together until dry.

Other Information

This product is insoluble in water. Dispose of used wipe in trash, do not flush into toilet.

Inactive Ingredients

Water

U.S. Distributor:
Sonora Corp.
1941 W Mission Blvd.
Pomona, CA 91766

Product of China